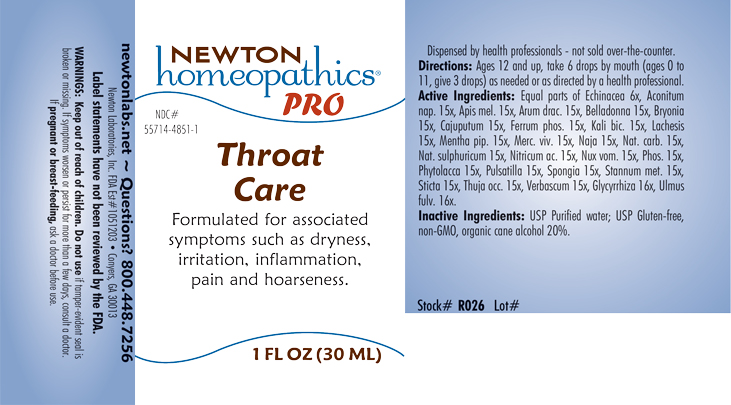 DRUG LABEL: Throat Care
NDC: 55714-4851 | Form: LIQUID
Manufacturer: Newton Laboratories, Inc.
Category: homeopathic | Type: HUMAN OTC DRUG LABEL
Date: 20240201

ACTIVE INGREDIENTS: PHYTOLACCA AMERICANA ROOT 15 [hp_X]/1 mL; ANEMONE PULSATILLA 15 [hp_X]/1 mL; BRYONIA ALBA ROOT 15 [hp_X]/1 mL; ECHINACEA, UNSPECIFIED 6 [hp_X]/1 mL; ACONITUM NAPELLUS 15 [hp_X]/1 mL; APIS MELLIFERA 15 [hp_X]/1 mL; ULMUS RUBRA BARK 16 [hp_X]/1 mL; CAJUPUT OIL 15 [hp_X]/1 mL; MERCURY 15 [hp_X]/1 mL; NAJA NAJA VENOM 15 [hp_X]/1 mL; POTASSIUM DICHROMATE 15 [hp_X]/1 mL; LACHESIS MUTA VENOM 15 [hp_X]/1 mL; MENTHA PIPERITA 15 [hp_X]/1 mL; SODIUM CARBONATE 15 [hp_X]/1 mL; SODIUM SULFATE 15 [hp_X]/1 mL; NITRIC ACID 15 [hp_X]/1 mL; STRYCHNOS NUX-VOMICA WHOLE 15 [hp_X]/1 mL; PHOSPHORUS 15 [hp_X]/1 mL; SPONGIA OFFICINALIS SKELETON, ROASTED 15 [hp_X]/1 mL; LOBARIA PULMONARIA 15 [hp_X]/1 mL; THUJA OCCIDENTALIS LEAFY TWIG 15 [hp_X]/1 mL; FERROSOFERRIC PHOSPHATE 15 [hp_X]/1 mL; GLYCYRRHIZA GLABRA 16 [hp_X]/1 mL; TIN 15 [hp_X]/1 mL; VERBASCUM THAPSUS 15 [hp_X]/1 mL; ARISAEMA DRACONTIUM ROOT 15 [hp_X]/1 mL; ATROPA BELLADONNA 15 [hp_X]/1 mL
INACTIVE INGREDIENTS: ALCOHOL; WATER

Throat 4851L

INDICATIONS AND USAGE SECTION

Formulated for associated symptoms such as dryness, irritation, inflammation, pain and hoarseness.

DOSAGE & ADMINISTRATION SECTION

Directions: Ages 12 and up, take 6 drops by mouth (ages 0 to 11, give 3 drops) as needed or as directed by a health professional.

OTC - ACTIVE INGREDIENT SECTION

Equal parts of Echinacea 6x, Aconitum nap. 15x, Apis mel. 15x, Arum drac. 15x, Belladonna 15x, Bryonia 15x, Cajuputum 15x, Ferrum phos. 15x, Glycyrrhiza 16x, Kali bic. 15x, Lachesis 15x, Menta pip. 15x, Merc. viv. 15x, Naja 15x, Nat. carb. 15x, Nat. sulphuricum 15x, Nitricum ac. 15x, Nux vom. 15x, Phos. 15x, Phytolacca 15x, Pulsatilla 15x, Spongia 15x, Stannum met. 15x, Sticta 15x, Thuja occ. 15x, Ulmus fulv. 16x, Verbascum 15x.

OTC - PURPOSE SECTION

Formulated for associated symptoms such as dryness, irrtiation, inflammation, pain and hoarseness.

INACTIVE INGREDIENT SECTION

USP Purified water; USP Gluten-free, non-GMO, organic cane alcohol 20%

QUESTIONS SECTION

newtonlabs.net – Questions? 800.448.7256

Newton Laboratories, Inc. FDA Est # 1051203 - Conyers, GA 30013

WARNINGS SECTION

WARNINGS: Keep out of reach of children. Do not use if tamper-evident seal is broken or missing. If symptoms worsen or persist for more than a few days, consult a doctor. If pregnant or breast-feeding, ask a doctor before use.

OTC - PREGNANCY OR BREAST FEEDING SECTION

If pregnant or breast-feeding, ask a doctor before use.

OTC - KEEP OUT OF REACH OF CHILDREN SECTION

WARNINGS: Keep out of reach of children.